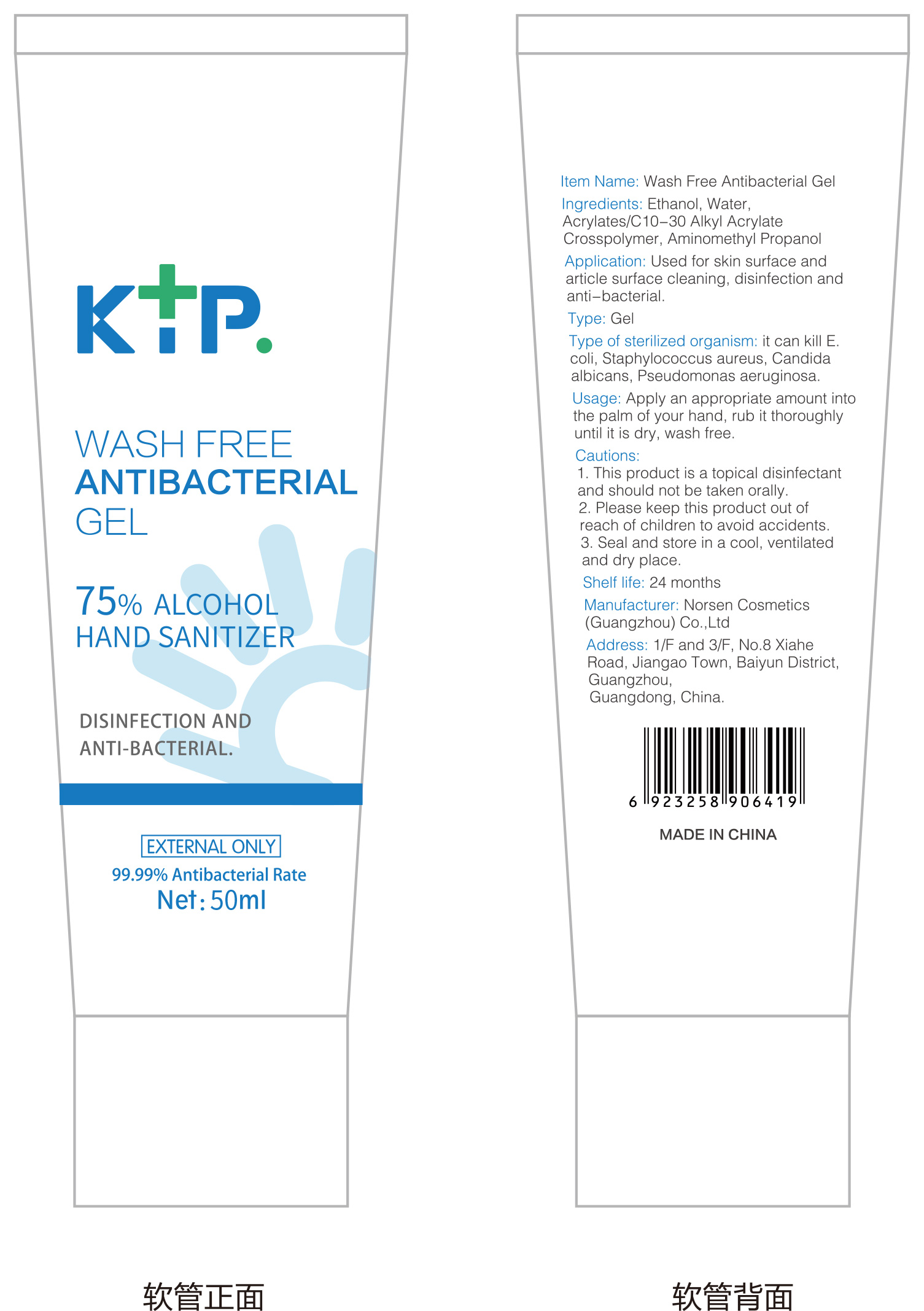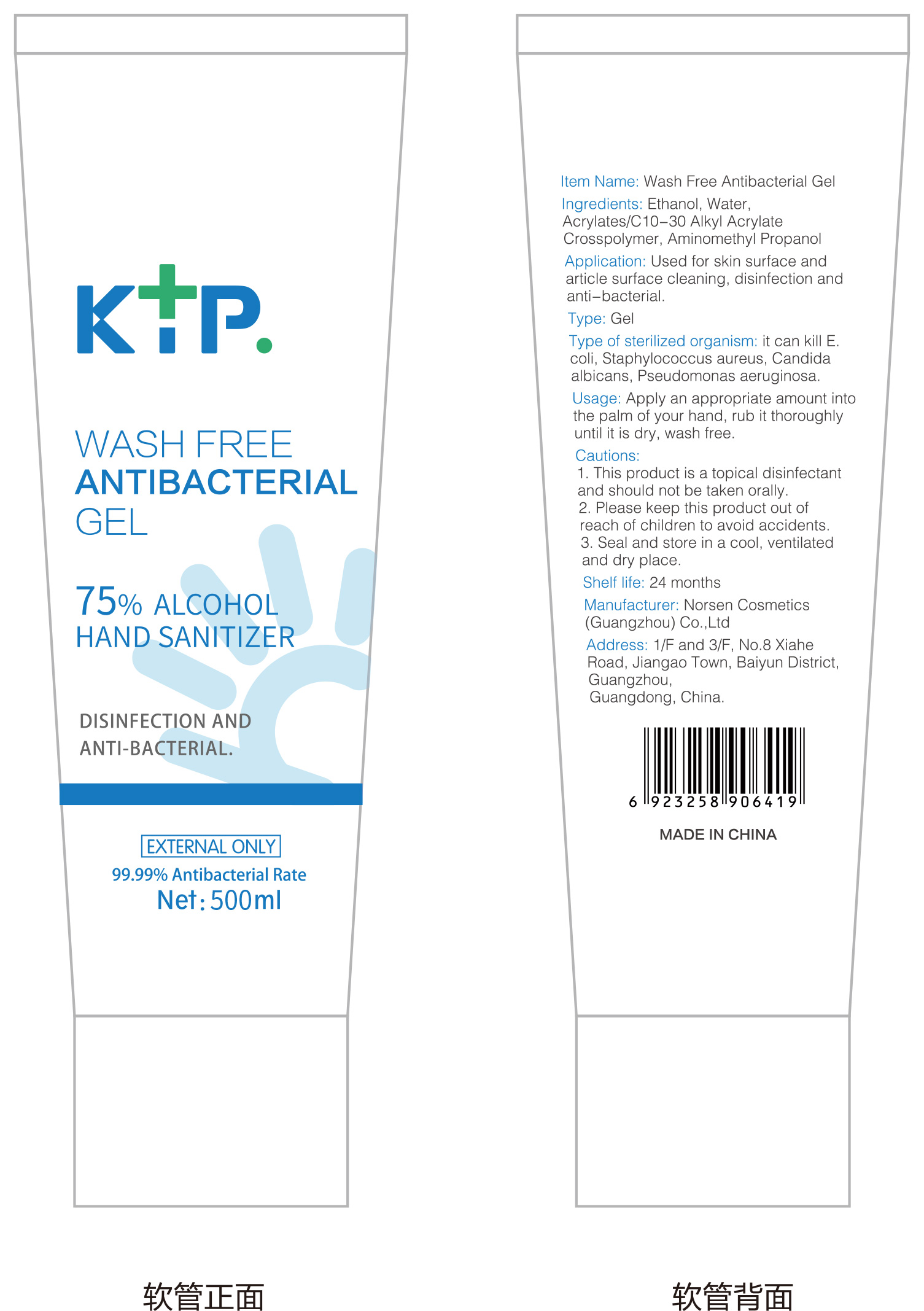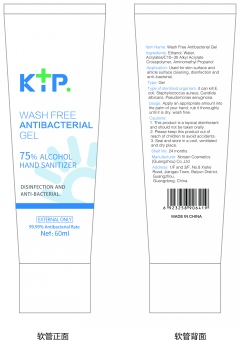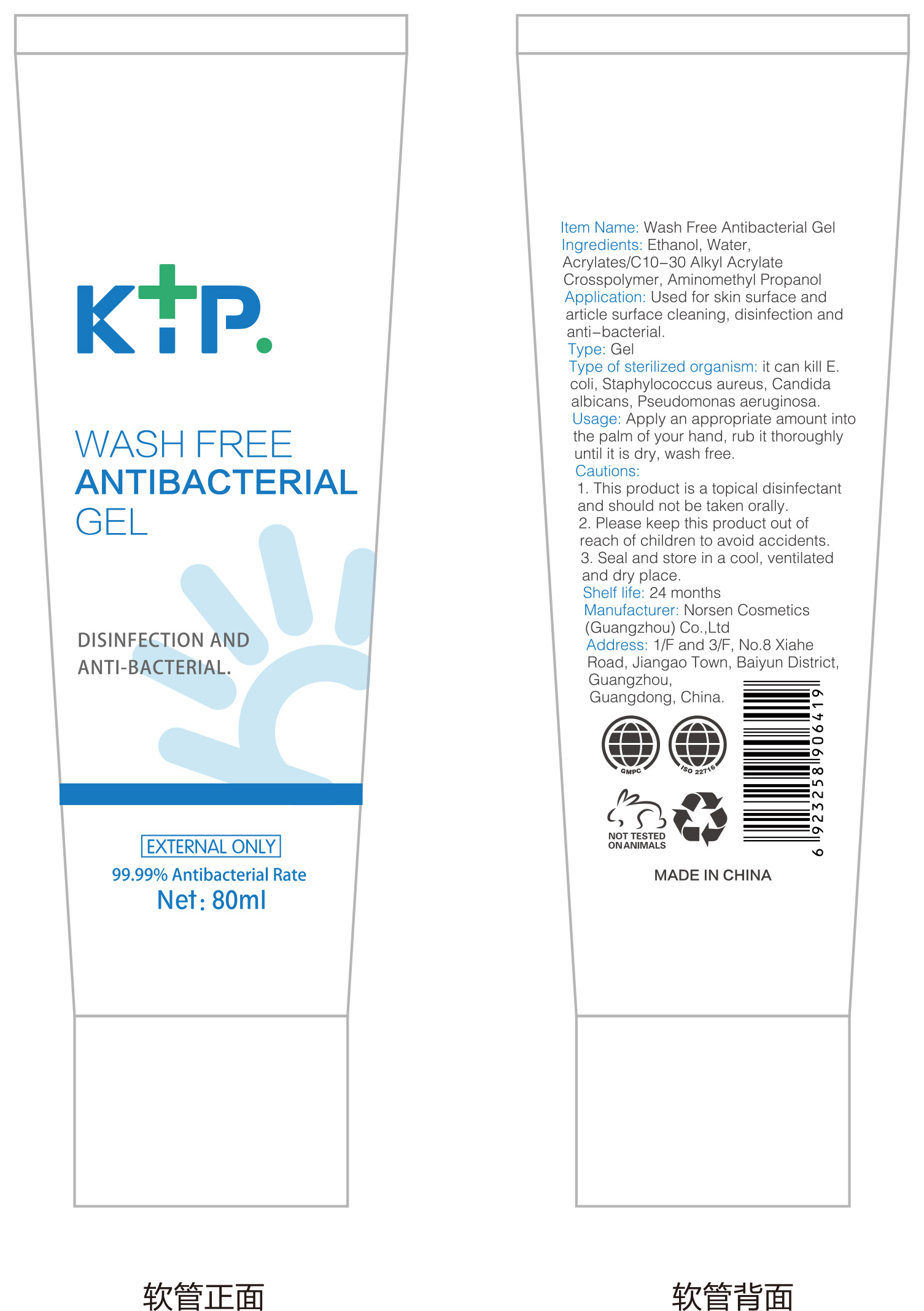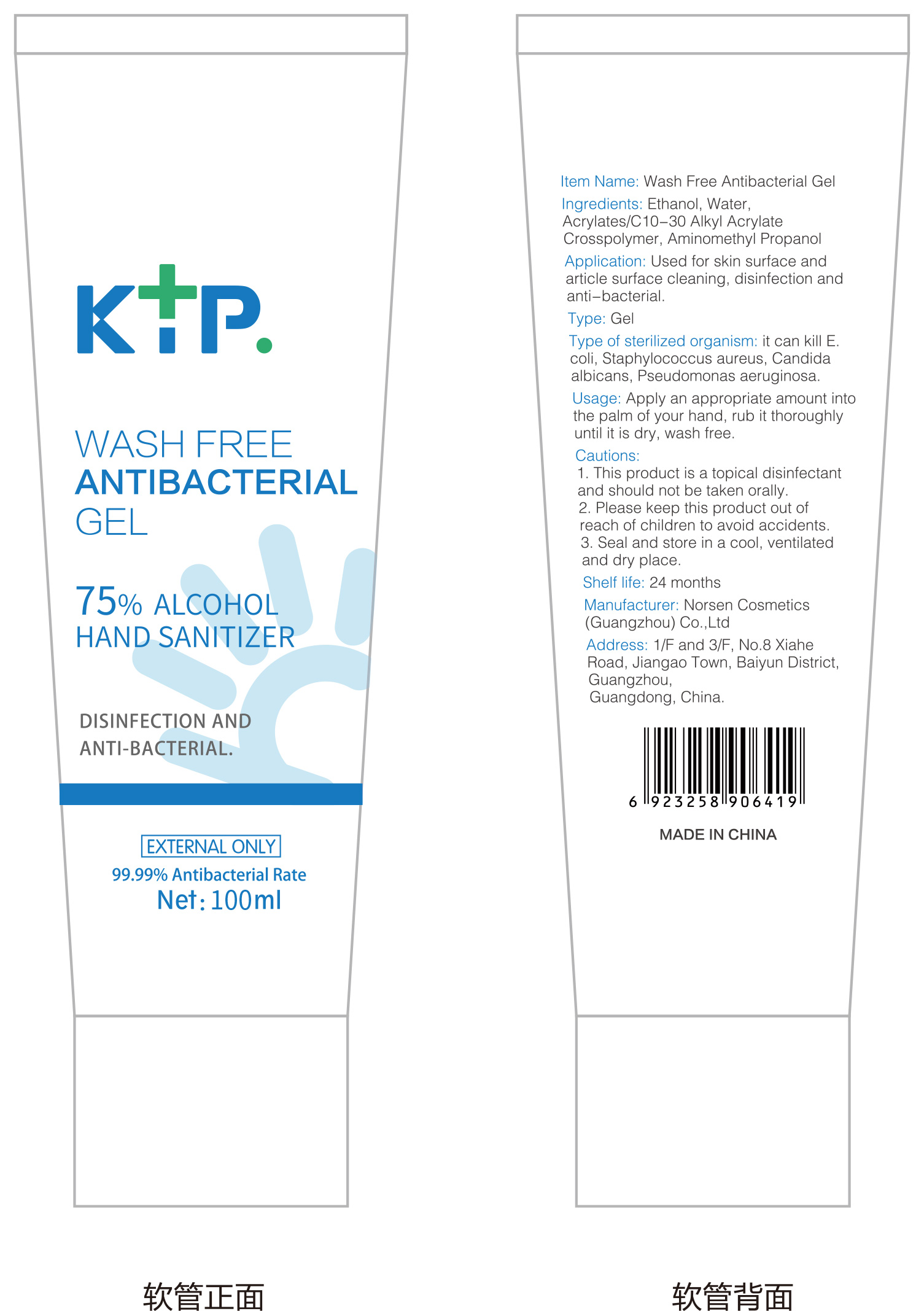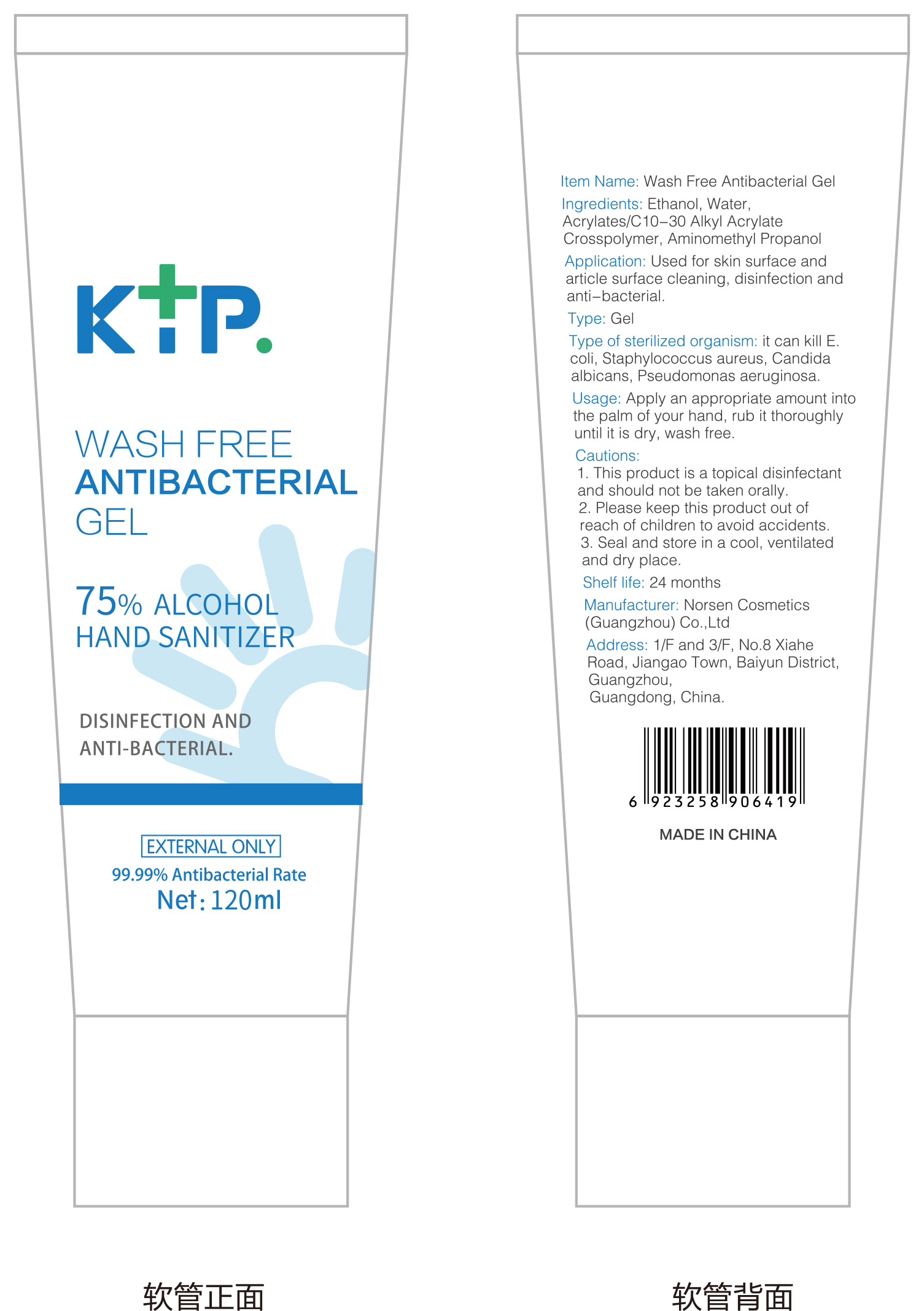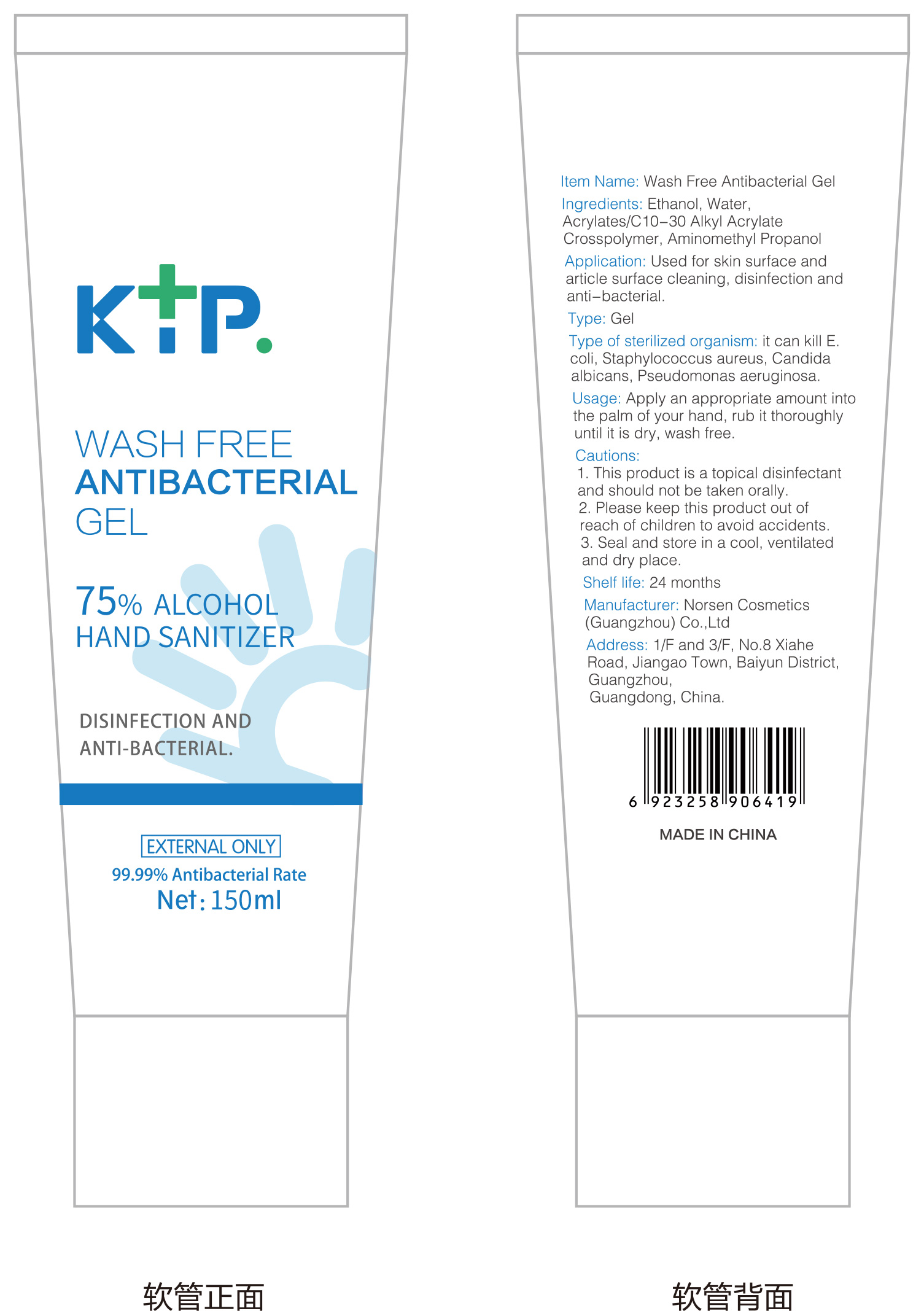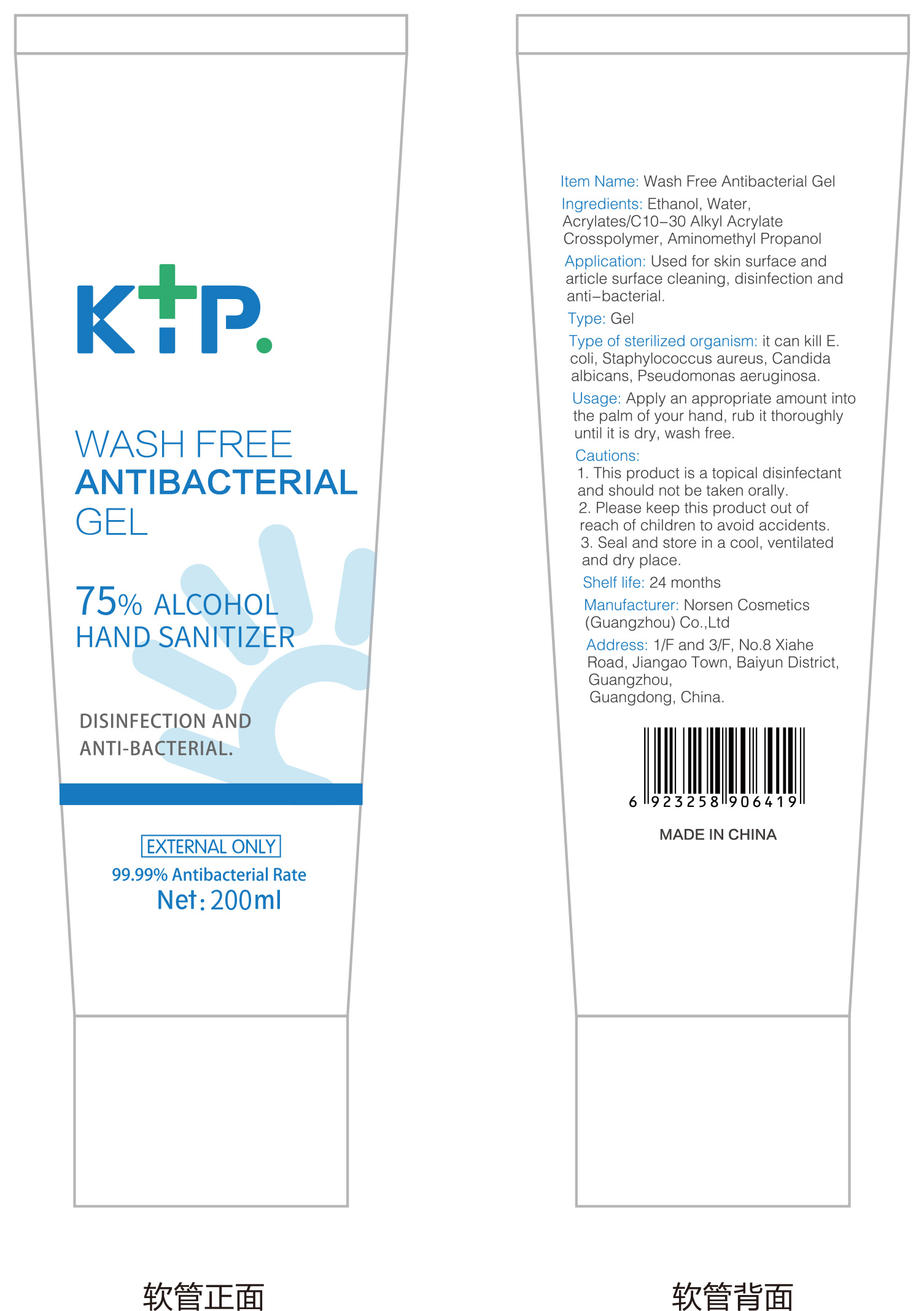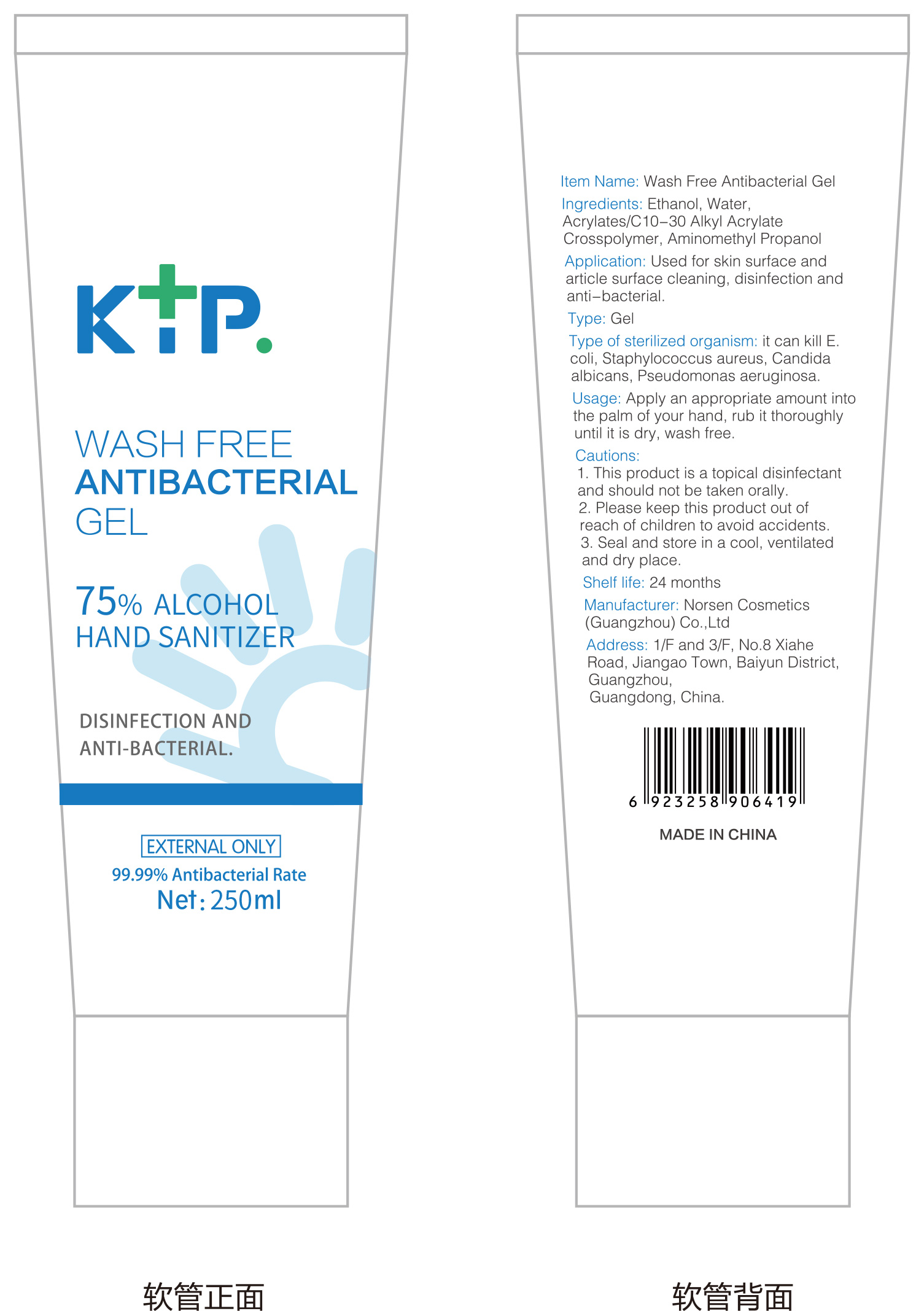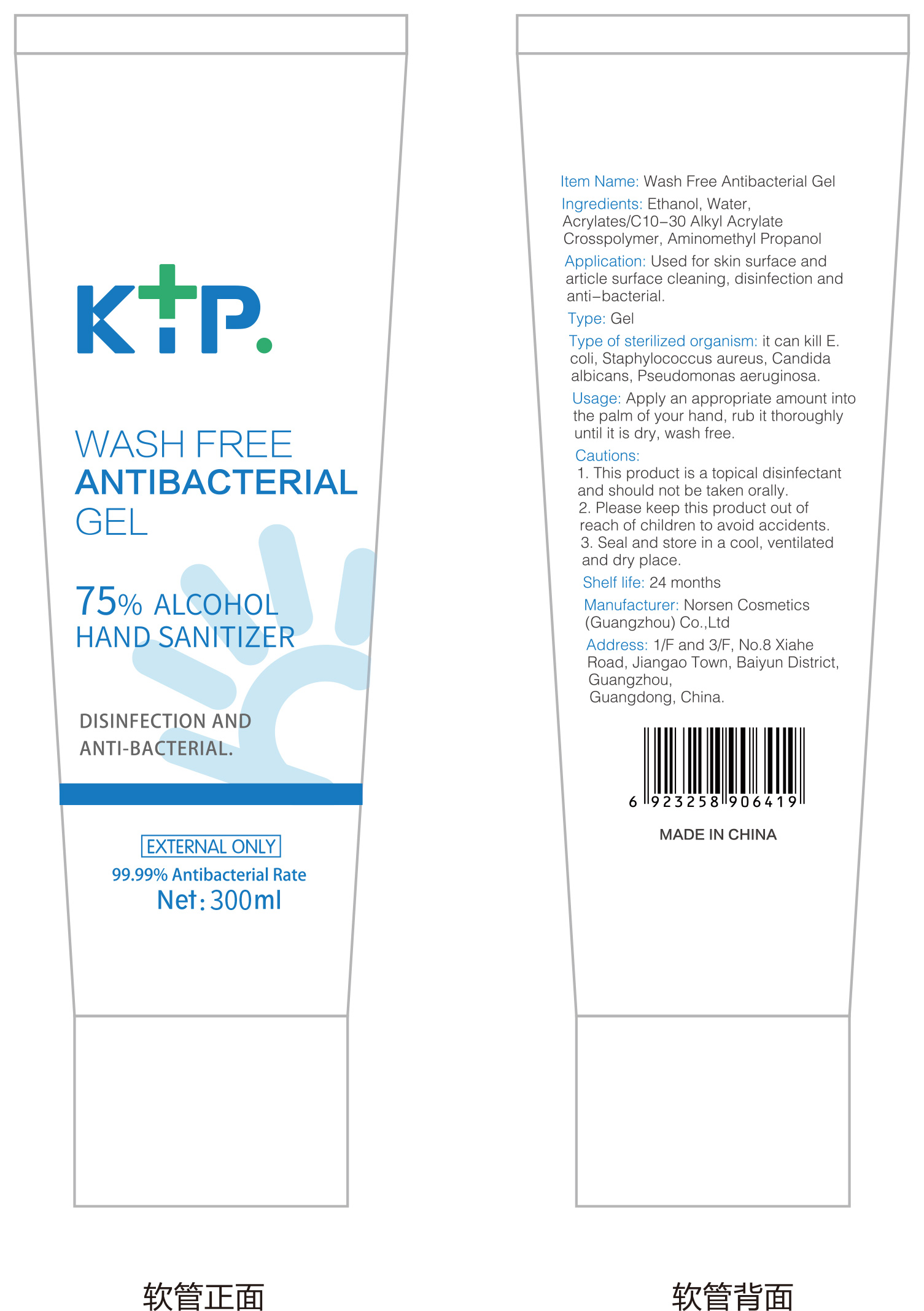 DRUG LABEL: Wash Free Antibacterial Gel
NDC: 75361-001 | Form: GEL
Manufacturer: Norsen Cosmetics (Guangzhou) Co., Ltd.
Category: otc | Type: HUMAN OTC DRUG LABEL
Date: 20200419

ACTIVE INGREDIENTS: ALCOHOL 75 mL/100 mL
INACTIVE INGREDIENTS: WATER; CARBOMER INTERPOLYMER TYPE A (ALLYL SUCROSE CROSSLINKED); AMINOMETHYLPROPANOL

Wash Free Antibacterial Gel

Active Ingredient

75% ALCOHOL

Usage

Apply an appropriate amount into the palm of your hand, rub it thoroughly

until it is dry,wash free.

Directions

1.This product is a topical disinfectant and should not be taken orally.

2.Please keep this product out of reach of children to avoid accidents.

3.Seal and store in a cool, ventilated and dry place.

Other information

it can kill E.coli,Staphylococcus aureus, Candida

albicans, Pseudomonas aeruginosa.

Inactive ingredients

Water,Acrylates/C10-30 Alkyl Acrylate Crosspolymer, Aminomethyl Propanol.